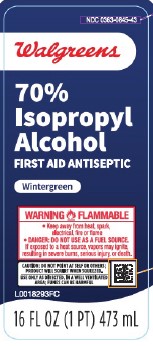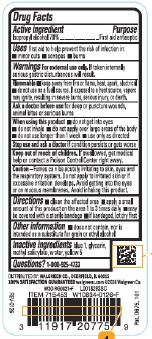 DRUG LABEL: 70% Rubbing
NDC: 0363-0845 | Form: LIQUID
Manufacturer: Walgreens Co.
Category: otc | Type: HUMAN OTC DRUG LABEL
Date: 20260205

ACTIVE INGREDIENTS: ISOPROPYL ALCOHOL 70 mL/100 mL
INACTIVE INGREDIENTS: FD&C BLUE NO. 1; GLYCERIN; METHYL SALICYLATE; WATER; FD&C YELLOW NO. 5

Walgreens 845.003/845AE
70% IPA, Wintergreen

Active ingredient

Isopropyl alcohol 70%

Purpose

First aid antiseptic

Use

first aid to help prevent the risk of infection in:

- minor cuts
- scrapes
- burns

Warnings

For external use only. If taken internally serious gastric disturbances will result.

Flammable.

- Keep away from fire or flame, heat, spark, electrical.
- do not use as a fuel source. If exposed to a heat source, vapors may ignite, resulting in severe burns, serious injury, or death.

Ask a doctor before use

for deep or puncture wounds, animal bites or serious burns

When using this product

- do not get into eyes
- do not inhale
- do not apply over large areas of the body
- do not use longer than 1 week
- use only as directed

Stop use and ask a doctor if

condition persists or gets worse

Keep out of reach of children.

If swallowed, get medical help or contact a Poison Control Center right away.

Caution

Fumes can be acutely irritating to skin, eyes and the respiratory system. Do not apply to irritated skin or if excessive irritation develops. Avoid getting into the eyes or on mucous membranes. Avoid inhaling this product.

Directions

- clean the affected area
- apply a small amount of the is product on the affected area 1 to 3 times daily
- may be covered with a sterile bandage
- if bandaged, let dry first

Other Information

- does not contain, nor is intended as a substitute for grain or ethyl alcohol

Inactive ingredients

blue 1, glycerin, methyl salicylate, water, yellow 5

Questions?

1-800-925-4733

ADVERSE REACTION

DISTRIBUTED BY: WALGREEN CO., DEERFIELD, IL 60015

100% SATISFACTION GUARANTEED walgreens.com ©2026 Walgreen Co.

Pat. D675, 101

Principal Display panel

NDC 0363-0845-43

Walgreens

70% Isopropyl Alcohol

First Aid Antiseptic

Wintergreen

WARNING FLAMMABLE

- Keep away from heat, spark, electrical, fire or flame
- DANGER: DO NOT USE AS A FUEL SOURCE.

If exposed to a heat source, vapors may ignite, resulting in severe burns, serious injury, or death.

CAUTION: DO NOT POINT AT SELF OR OTHERS; PRODUCT WILL SQUIRT WHEN SQUEEZED.

USE ONLY AS DIRECTED, IN A WELL-VENTILATED AREA; FUMES MAY BE HARMFUL.

16 FL OZ (1 PT) 473 mL